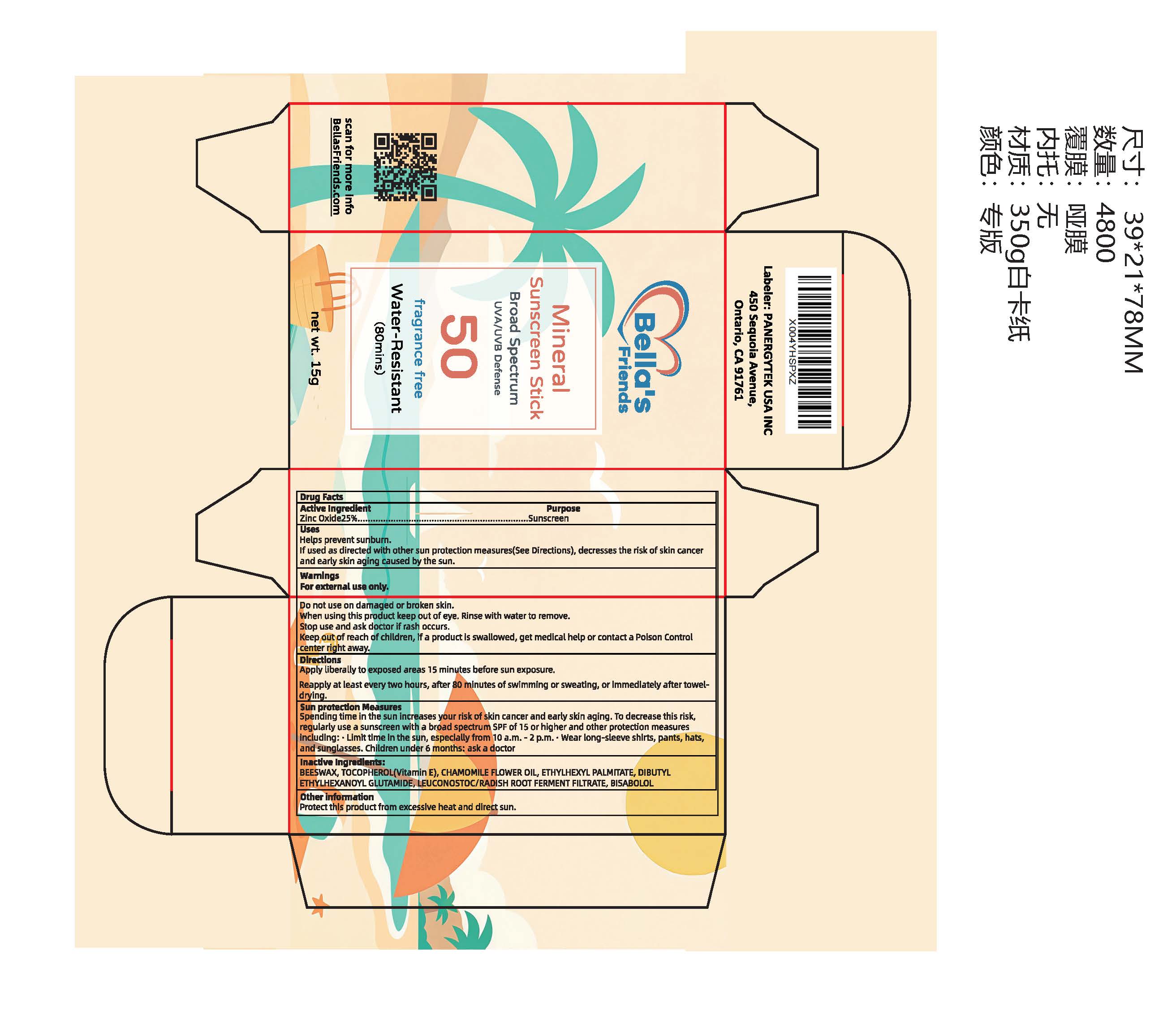 DRUG LABEL: Bellas Friends Sunscreen Stick
NDC: 85950-003 | Form: PASTE
Manufacturer: Panergytek Usa Inc
Category: otc | Type: HUMAN OTC DRUG LABEL
Date: 20260104

ACTIVE INGREDIENTS: ZINC OXIDE 25 g/100 g
INACTIVE INGREDIENTS: 1,2-HEXANEDIOL; WATER; ETHYLHEXYL PALMITATE; BISABOLOL; LEUCONOSTOC/RADISH ROOT FERMENT FILTRATE; TOCOPHEROL; CHAMOMILE FLOWER OIL; BEESWAX; DIBUTYL ETHYLHEXANOYL GLUTAMIDE; ALPHA-TOCOPHEROL ACETATE

85950-003-01 Bella's Friends Sunscreen Stick

Active Ingredient
Zinc Oxide25%...
Purpose
..Sunscreen

PURPOSE

Helps prevent sunburn.
If used as directed with other sun protection measures(See Directions), decresses the risk of skin cancer
and early skin aging caused by the sun.

Keep out of reach of children,if a product is swallowed, get medical help or contact a Poison Control
center right away.

Warnings
For external use only.
Do not use on damaged or broken skin.
When using this product keep out of eye. Rinse with water to remove.
Stop use and ask doctor if rash occurs.

INDICATIONS AND USAGE

Apply liberally to exposed areas 15 minutes before sun exposure.
Reapply at least every two hours, after 80 minutes of swimming or sweating, or immediately after towel-
drying.

DOSAGE AND ADMINISTRATION

Sun protection MeasuresSpending time in the sun increases your risk of skin cancer and early skin aging.To decrease this risk,'egularly use a sunscreen with a broad spectrum SPF of 15 or higher and other protection measuresincluding: .Limit time in the sun, especially from 10 a.m. - 2 p.m..Wear long-sleeve shirts, pants, hatand sunglasses. Children under 6 months: ask a doctor

Inactive Ingredients:
BEESWAX, TOCOPHEROL(Vitamin E), CHAMOMILE FLOWER OIL, ETHYLHEXYL PALMITATE, DIBUTYLETHYLHEXANOYL GLUTAMIDE, LEUCONOSTOC/RADISH ROOT FERMENT FILTRATE, BISABOLOL